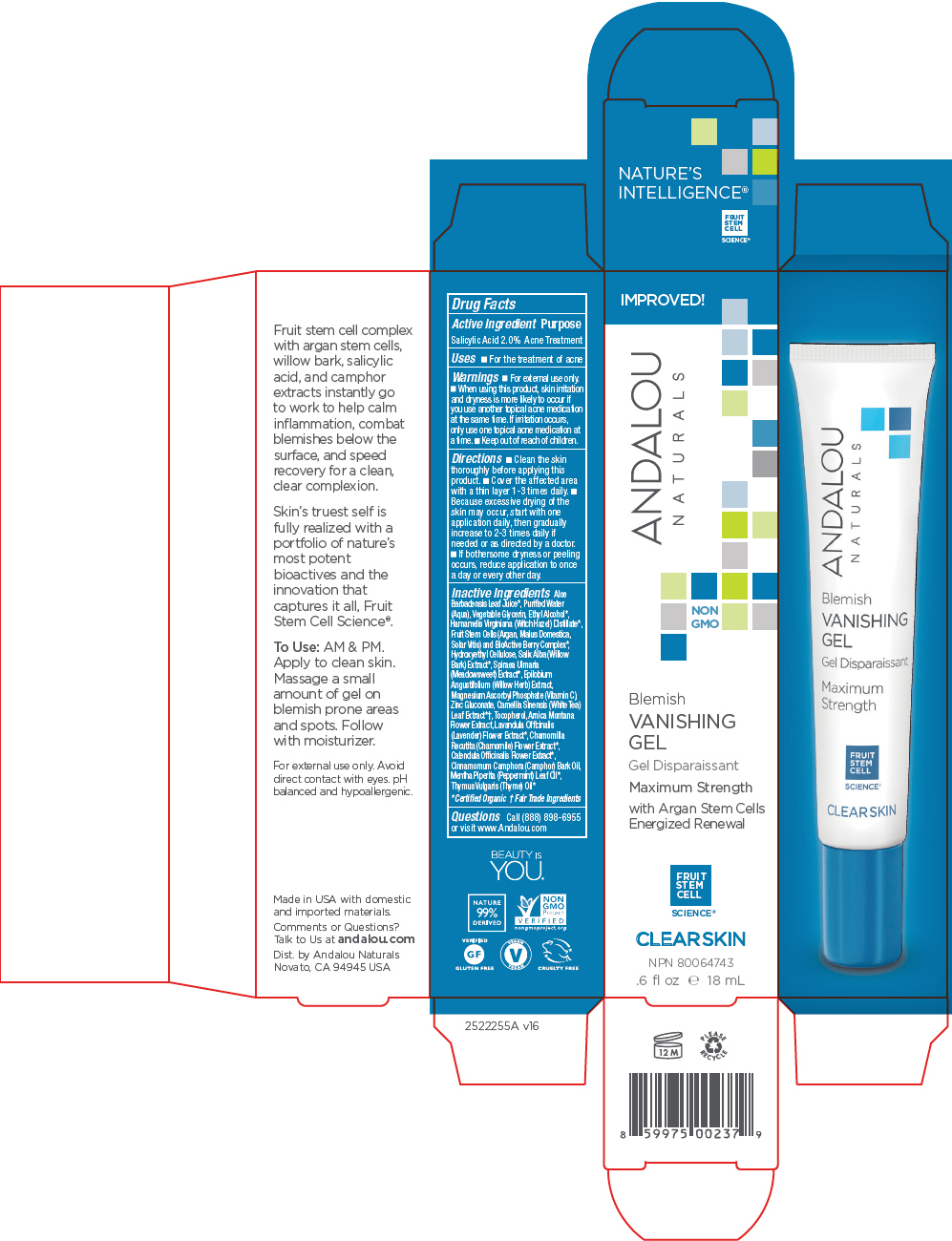 DRUG LABEL: Blemish Vanishing
NDC: 55560-1810 | Form: GEL
Manufacturer: Andalou naturals
Category: otc | Type: HUMAN OTC DRUG LABEL
Date: 20190905

ACTIVE INGREDIENTS: SALICYLIC ACID 20 mg/1 mL
INACTIVE INGREDIENTS: ALOE VERA LEAF; WATER; GLYCERIN; ALCOHOL; WITCH HAZEL; ARGANIA SPINOSA SEED; APPLE; VITIS VINIFERA SEED; ACAI; ARONIA MELANOCARPA FRUIT JUICE; ARCTOSTAPHYLOS UVA-URSI LEAF; VACCINIUM MYRTILLUS ANTHOCYANOSIDES; EUROPEAN ELDERBERRY JUICE; LYCIUM BARBARUM FRUIT; ROSA CANINA FRUIT; HIPPOPHAE RHAMNOIDES FRUIT; HYDROXYETHYL CELLULOSE (100 MPA.S AT 2%); WILLOW BARK; FILIPENDULA ULMARIA FLOWER; EPILOBIUM ANGUSTIFOLIUM FLOWERING TOP; MAGNESIUM ASCORBYL PHOSPHATE; ZINC GLUCONATE; WHITE TEA; TOCOPHEROL; ARNICA MONTANA FLOWER; LAVANDULA ANGUSTIFOLIA SUBSP. ANGUSTIFOLIA FLOWER; CHAMOMILE; CALENDULA OFFICINALIS FLOWER; CAMPHOR OIL, WHITE; PEPPERMINT OIL; THYME OIL

Blemish Vanishing Gel

Drug Facts

Active Ingredient

Salicylic Acid 2.0%

Purpose

Acne Treatment

Uses

- For the treatment of acne

Warnings

- For external use only.
- When using this product, skin irritation and dryness is more likely to occur if you use another topical acne medication at the same time. If irritation occurs, only use one topical acne medication at a time.

- Keep out of reach of children.

Directions

- Clean the skin thoroughly before applying this product.
- Cover the affected area with a thin layer 1-3 times daily.
- Because excessive drying of the skin may occur, start with one application daily, then gradually increase to 2-3 times daily if needed or as directed by a doctor.
- If bothersome dryness or peeling occurs, reduce application to once a day or every other day.

Inactive Ingredients

Aloe Barbadensis Leaf Juice [Certified Organic] , Purified Water (Aqua), Vegetable Glycerin, Ethyl Alcohol, Hamamelis Virginiana (Witch Hazel) Distillate, Fruit Stem Cells (Argan, Malus Domestica, Solar Vitis) and BioActive Berry Complex, Hydroxyethyl Cellulose, Salix Alba (Willow Bark) Extract, Spiraea Ulmaria (Meadowsweet) Extract, Epilobium Angustifolium (Willow Herb) Extract, Magnesium Ascorbyl Phosphate (Vitamin C), Zinc Gluconate, Camellia Sinensis (White Tea) Leaf Extract [Fair Trade Ingredients] , Tocopherol, Arnica Montana Flower Extract, Lavandula Officinalis (Lavender) Flower Extract, Chamomilla Recutita (Chamomile) Flower Extract, Calendula Officinalis Flower Extract, Cinnamomum Camphora (Camphor) Bark Oil, Mentha Piperita (Peppermint) Leaf Oil, Thymus Vulgaris (Thyme) Oil

Questions

Call (888) 898-6955 or visit www.Andalou.com

Dist. by Andalou Naturals
Novato, CA 94945 USA

PRINCIPAL DISPLAY PANEL - 18 mL Tube Carton

IMPROVED!

ANDALOU
NATURALS

NON
GMO

Blemish
VANISHING
GEL

Maximum Strength

with Argan Stem Cells
Energized Renewal

FRUIT
STEM
CELL
SCIENCE®

CLEARSKIN

NPN 80064743

.6 fl oz e 18 mL